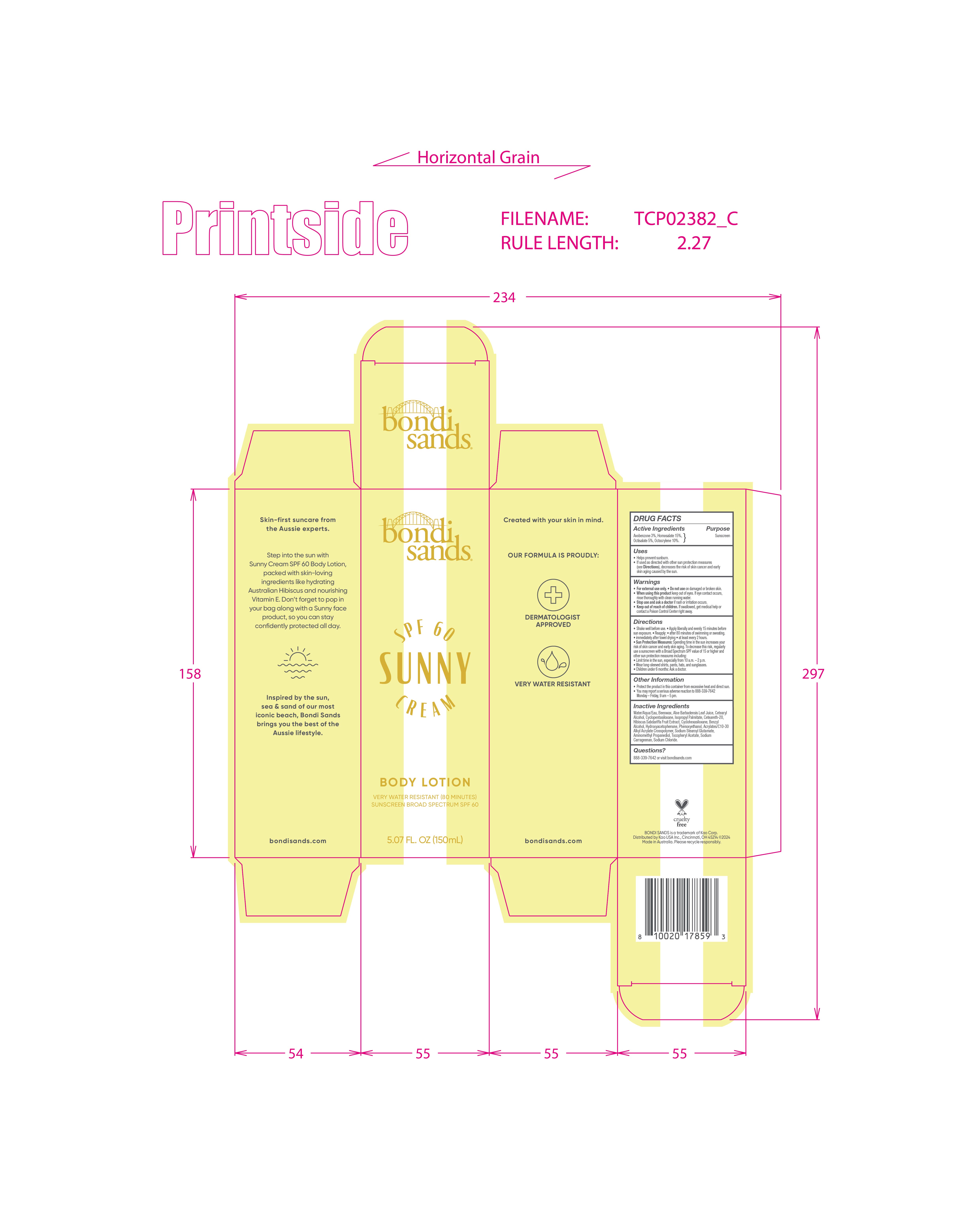 DRUG LABEL: Bondi Sands Broad Spectrum SPF 60 Sunny Cream Body
NDC: 70157-021 | Form: LOTION
Manufacturer: Baxter Laboratories Pty. Ltd.
Category: otc | Type: HUMAN OTC DRUG LABEL
Date: 20251023

ACTIVE INGREDIENTS: OCTISALATE 5 g/100 mL; HOMOSALATE 15 g/100 mL; OCTOCRYLENE 10 g/100 mL; AVOBENZONE 3 g/100 mL
INACTIVE INGREDIENTS: BEESWAX; ISOPROPYL PALMITATE; CYCLOHEXASILOXANE; DISODIUM STEAROYL GLUTAMATE; CYCLOPENTASILOXANE; CETEARETH-20; .ALPHA.-TOCOPHEROL ACETATE; HYDROXYACETOPHENONE; ACRYLATES/C10-30 ALKYL ACRYLATE CROSSPOLYMER (60000 MPA.S); BENZYL ALCOHOL; SODIUM CARRAGEENAN; PHENOXYETHANOL; SODIUM CHLORIDE; WATER; HIBISCUS SABDARIFFA WHOLE; AMINOMETHYL PROPANEDIOL; ALOE VERA LEAF; CETEARYL ALCOHOL

Bondi Sands Broad Spectrum SPF 60 Sunny Cream Body Lotion

Active Ingredients

Avobenzone 3%

Homosalate 15%

Octisalate 5%

Octocrylene 10%

Purpose

Sunscreen

Keep out of reach of children. If swallowed, get medical help or contact a Poison Control Center right away.

Stop use and ask a doctor if rash or irritation occurs.

WARNINGS

- For external use only
- Do not use on damaged or broken skin
- When using this product keep out of eyes.If eye contact occurs, rinse thoroughly with clean running water.

Directions

- Shake well before use
- Apply liberally and evenly 15 minutes before sun exposure

Reapply

- after 80 minutes of swimming or sweating.
- immediately after towel drying
- at least every 2 hours

Sun Protection Measures: Spending time in the sun increases your risk of skin cancer and early skin aging. To decrease this risk, regularly use a sunscreen with a Broad Spectrum SPF value of 15 or higher and other sub and other sun protection measures including:

- Limit time in the sun, especially from 10 a.m.- 2 p.m.
- Wear long-sleeved shirts, pants, hats and sunglasses
- Children under 6 months: Ask a doctor

Inactive Ingredients

Water/Aqua/Eau, Beeswax, Aloe Barbadensis Leaf Juice, Cetearyl Alcohol, Cyclopentasiloxane, Isopropyl Palmitate, Ceteareth-20,

Hibiscus Sabdariffa Fruit Extract, Cyclohexasiloxane, Benzyl Alcohol, Hydroxyacetopenone, Phenoxyethanol, Acrylates/C10-30 Alkyl Acrylate Crosspolymer, Sodium Stearoyl Glutamate, Aminomethyl Propanediol, Tocopheryl Acetate, Sodium Carrageenan, Sodium Chloride.

PACKAGE LABEL

Bondi Sands

SPF 60

Sunny Cream

Body Lotion

5.07 FL. OZ (150mL)